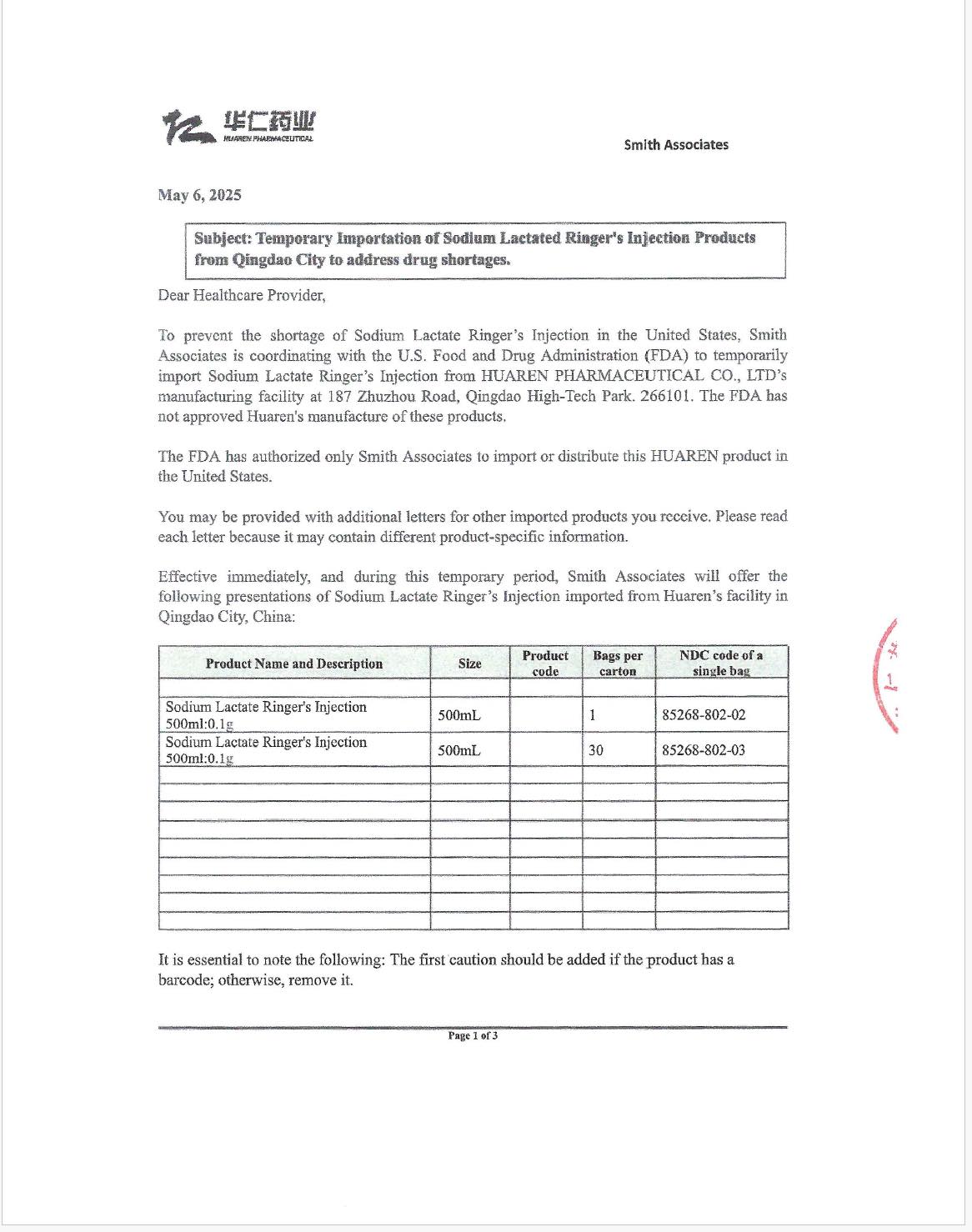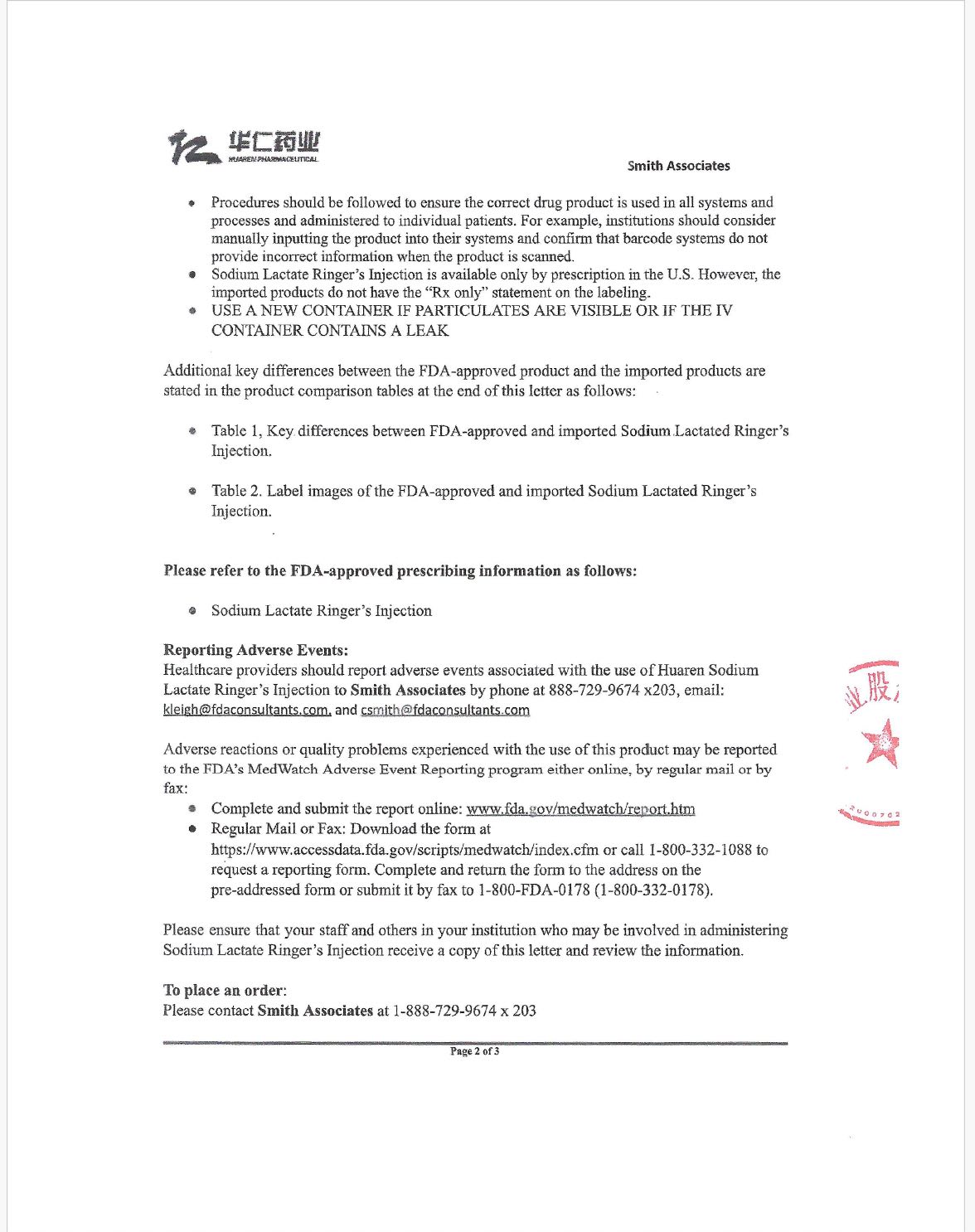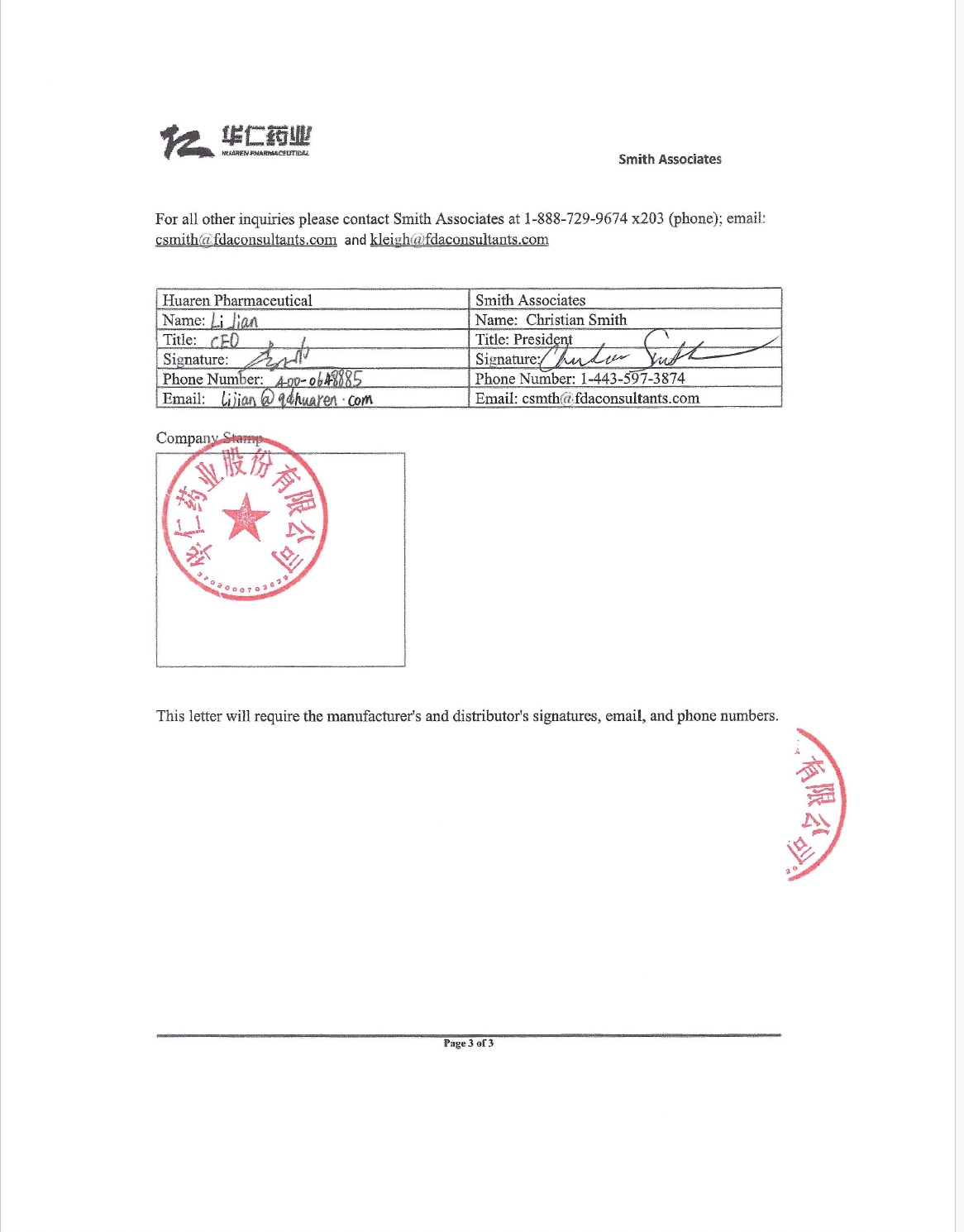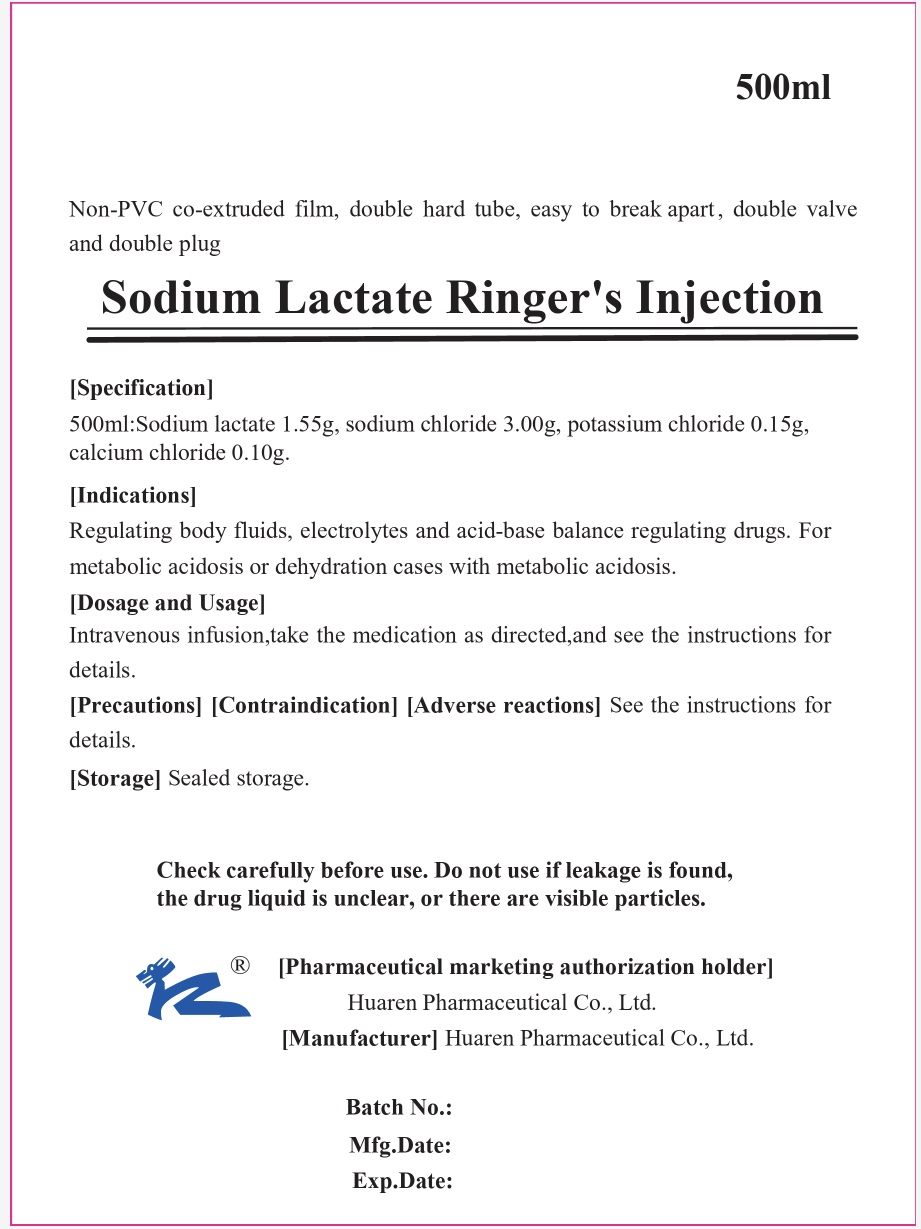 DRUG LABEL: LACTATED RINGER
NDC: 85268-802 | Form: INJECTION, SOLUTION
Manufacturer: Huaren Pharmaceutical Co., Ltd.
Category: prescription | Type: HUMAN PRESCRIPTION DRUG LABEL
Date: 20250826

ACTIVE INGREDIENTS: CALCIUM CHLORIDE 0.2 g/1000 mL; POTASSIUM CHLORIDE 0.3 g/1000 mL; SODIUM LACTATE 3.1 g/1000 mL; SODIUM CHLORIDE 6 g/1000 mL
INACTIVE INGREDIENTS: WATER

Lactate Ringer - Q (EUA)

SODIUM LACTATE RINGER'S INJECTION, USP BAG

Sodium Lactate Ringer's Injection Instructions

Please read the instructions carefully and use under the guidance of a physician.

Check carefully before use. Do not use if leakage is found, the drug liquid is unclear, or there are visible particles.

INGREDIENTS

This product is a compound preparation, its components are: sodium lactate 3.10g, sodium chloride 6.00g, potassium chloride 0.30g, calcium chloride (CaCl2·2H2O) 0.2g per 1000ml.

Excipient Name: Sodium Hydroxide

Osmotic Pressure Molar Concentration: 240-270mOsmol/kg

CHARACTER

This product is a colorless and clear liquid.

INDICATIONS

Regulating body fluids, electrolytes and acid-base balance regulating drugs. For metabolic acidosis or dehydration cases with metabolic acidosis.

SPECIFICATION

- 500ml
- 1000ml: Sodium lactate 3.10g, sodium chloride 6.00g, potassium chloride 0.30g, calcium chloride 0.20g.

DOSAGE AND USAGE

Intravenous drip. Adult 500ml ~ 1000ml at a time, according to age weight and symptoms can be appropriate to increase or decrease. Administration speed: 300 ~ 500ml per hour for adults.

ADVERSE REACTIONS

- Patients with hypocalcemia (such as uremia) are prone to numbness, pain, twitching, dyspnea and other symptoms after correcting acidosis, which are often caused by the decrease of calcium ion concentration in the blood;
- Accelerated heart rate, chest tightness, shortness of breath and other pulmonary edema, heart failure;
- Elevated blood pressure;
- Weight gain, edema;
- Alkalosis occurs when overdose;
- The concentration of blood potassium decreases, and sometimes hypokalemia appears.

CONTRAINDICATION

The following conditions should be contraindicated:

- Heart failure and acute pulmonary edema;
- Cerebral edema;
- Lactic acidosis;
- Severe hepatic insufficiency;
- Severe renal failure oliguria or anuria;
- Hyperkalemia;
- Severe burn;
- Addison's disease.

PRECAUTIONS

The following cases should be used with caution:

- Diabetic patients taking biguanides (especially hypoglycemic), hinder the liver's utilization of lactic acid, easy to cause lactic acid poisoning;
- Edema patients with a tendency to sodium retention;
- Hypertension patients can increase blood pressure;
- Heart dysfunction;
- The rate of lactic acid degradation is slowed down when liver function is not complete, so as to delay the correction speed of acidosis;
- Hypoxia and shock, insufficient tissue blood supply and hypoxia when lactic acid oxidation into pyruvate into tricarboxylic acid cycle metabolism slowed down, so as to delay the correction speed of acidosis;
- Alcoholism, salicylic acid poisoning, type I glycogen deposition disease have lactic acidosis tendency, it is not appropriate to use sodium lactate to correct the acid-base balance;
- When diabetic ketoacidosis acetoacetic acid, β-hydroxybutyric acid and lactic acid are increased, and often accompanied by poor circulation or insufficient blood supply of organs, lactic acid degradation rate is slowed down;
- Renal insufficiency, prone to water and sodium retention, increase cardiovascular load.

The following tests and observations should be made during medication:

- Blood pH and/or carbon dioxide binding force;
- Serum sodium, potassium, calcium, chlorine concentration determination;
- Determination of renal function, including creatinine, urea nitrogen, etc.;
- Blood pressure;
- Cardiopulmonary function status, such as edema, shortness of breath, cyanosis, pulmonary rale, jugular vein filling, hepato-jugular vein regurgitation, venous pressure or central venous pressure measurement as needed;
- Liver insufficiency performance jaundice, change of mind, ascites, etc., applied before and after sodium lactate and in the application process, often observed at any time.

MEDICATION IN PREGNANT WOMEN AND LACTATING WOMEN

Pregnant women with gestational poisoning may aggravate edema, increase blood pressure, should be used with caution.

MEDICATION IN CHILDREN

The dosage should be calculated according to age, weight and condition.

MEDICATION IN THE ELDERLY

Elderly patients often have hidden cardiac and renal insufficiency, which should be used with caution.

DRUG INTERACTIONS

When combined with other drugs, pay attention to the incompatibility of drugs (such as macrolide antibiotics, alkaloids, sulfonamides) due to changes in pH and ionic strength. Because this product contains calcium ions, it will precipitate when mixed with blood containing sodium citra

DRUG OVERDOSE

An overdose may result in edema or ion imbalance in the body.

PHARMACOLOGY AND TOXICOLOGY

This product can regulate body fluid volume and osmotic pressure, and can supplement potassium, sodium, calcium and chloride ions. Among them, sodium lactate is converted into bicarbonate ion in the body to regulate acid-base balance and maintain normal physiological functions; Na＋is the most important cation in extracellular fluid, which is the main substance for maintaining constant osmotic pressure and extracellular volume of body fluid. K＋is the main intracellular cation, which plays an important role in maintaining normal neuromuscular excitability. As a second messenger in the cell, calcium ion is closely related to many functions in the body. Lactate ions can correct metabolic acidosis and allow potassium ions to enter the cell from blood and extracellular fluid. When the amount of circulating blood and interstitial fluid in the body is reduced, this product can be used as a supplementary regulator of interstitial fluid, and has a corrective effect on electrolyte disturbance and acidosis.

PHARMACOKINETICS

This experiment has not been performed and no reliable references are available.

PACKAGE

1. Plastic infusion bag (non-PVC co-extruded film, double hard tube, easy to fold, double valve and double plug). 50ml/ bag, 100ml/ bag, 250ml/ bag, 500ml/ bag, 10O0ml/ bag.
2. Plastic infusion bag (non-PVC co-extruded film, double hard tube, easy to fold, double valve double plug, double aseptic packaging). 50ml/ bag, 100ml/ bag, 250ml/ bag, 500ml/ bag, 1000ml/ bag.

VALIDITY

1. The product of 50ml,100ml, and 1000ml specifications is valid for 24 months.
2. The validity period of 250ml,500ml is 36 months.

STORAGE

Sealed storage.

OTHER INFORMATION

[Package]

Plastic infusion bag (non-PVC co-extruded film, double hard tube, easy to break apart , double valve and double plug). 500ml/ bag, 1000ml/ bag.

[Validity] 24 months

[Executive standard] Pharmacopoeia of the People's Republic of China (2020, Volume II)

[Pharmaceutical marketing authorization holder] Name: Huaren Pharmaceutical Co., Ltd. Registered Address: No. 187, Zhuzhou Road, Qingdao High-tech Park,China

[Manufacturer]

Enterprise Name: Huaren Pharmaceutical Co., Ltd.

Production Address: No. 187, Zhuzhou Road, Qingdao High-tech Park,China

Zip code: 266101

Tel.: 400-0648885 0532-67709071

Fax: 0532-88702625

Website：http//www.qdhuaren.com